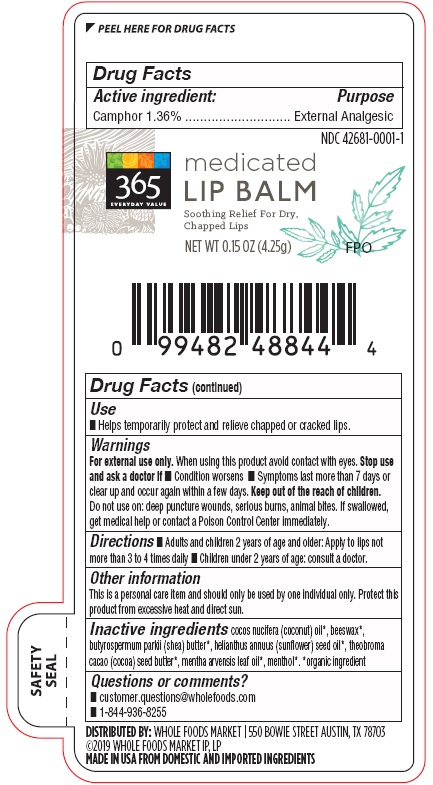 DRUG LABEL: 365 Medicated Lip Balm
NDC: 42681-0001 | Form: STICK
Manufacturer: Whole Foods Market, Inc.
Category: otc | Type: HUMAN OTC DRUG LABEL
Date: 20231103

ACTIVE INGREDIENTS: CAMPHOR (NATURAL) 0.0578 g/4.25 g
INACTIVE INGREDIENTS: COCONUT OIL; YELLOW WAX; SHEA BUTTER; SUNFLOWER OIL; COCOA BUTTER; MENTHA ARVENSIS LEAF OIL; MENTHOL

365 EVERYDAY VALUE Medicated Lip Balm

DRUG FACTS

Active ingredient:
Camphor 1.36%

Purpose
External Analgesic

Warnings
For external use only. When using this product avoid contact with eyes. Stop use
and ask a doctor if ■ Condition worsens ■ Symptoms last more than 7 days or
clear up and occur again within a few days. Keep out of the reach of children.
Do not use on: deep puncture wounds, serious burns, animal bites. If swallowed,
get medical help or contact a Poison Control Center immediately.

Keep out of the reach of children.

DOSAGE AND ADMINISTRATION

Directions■ Adults and children 2 years of age and older: Apply to lips not
more than 3 to 4 times daily ■ Children under 2 years of age: consult a doctor.

Other information
This is a personal care item and should only be used by one individual only. Protect this
product from excessive heat and direct sun.

Inactive ingredients cocos nucifera (coconut) oil*, beeswax*,
butyrospermum parkii (shea) butter*, helianthus annuus (sunflower) seed oil*, theobroma
cacao (cocoa) seed butter*, mentha arvensis leaf oil*, menthol*. *organic ingredient

Questions or comments?
■ customer.questions@wholefoods.com
■ 1-844-936-8255

Principal Display Package

NDC 42681-0001-1

365
EVERYDAY VALUE

medicated
LIP BALM

Soothing Relief For Dry,
Chapped Lips

NET WT 0.15 OZ (4.25g) FPO

0 99482 48844 4

DISTRIBUTED BY: WHOLE FOODS MARKET | 550 BOWIE STREET AUSTIN, TX 78703
©2019 WHOLE FOODS MARKET IP, LP
MADE IN USA FROM DOMESTIC AND IMPORTED INGREDIENTS

SAFETY
SEAL

rege